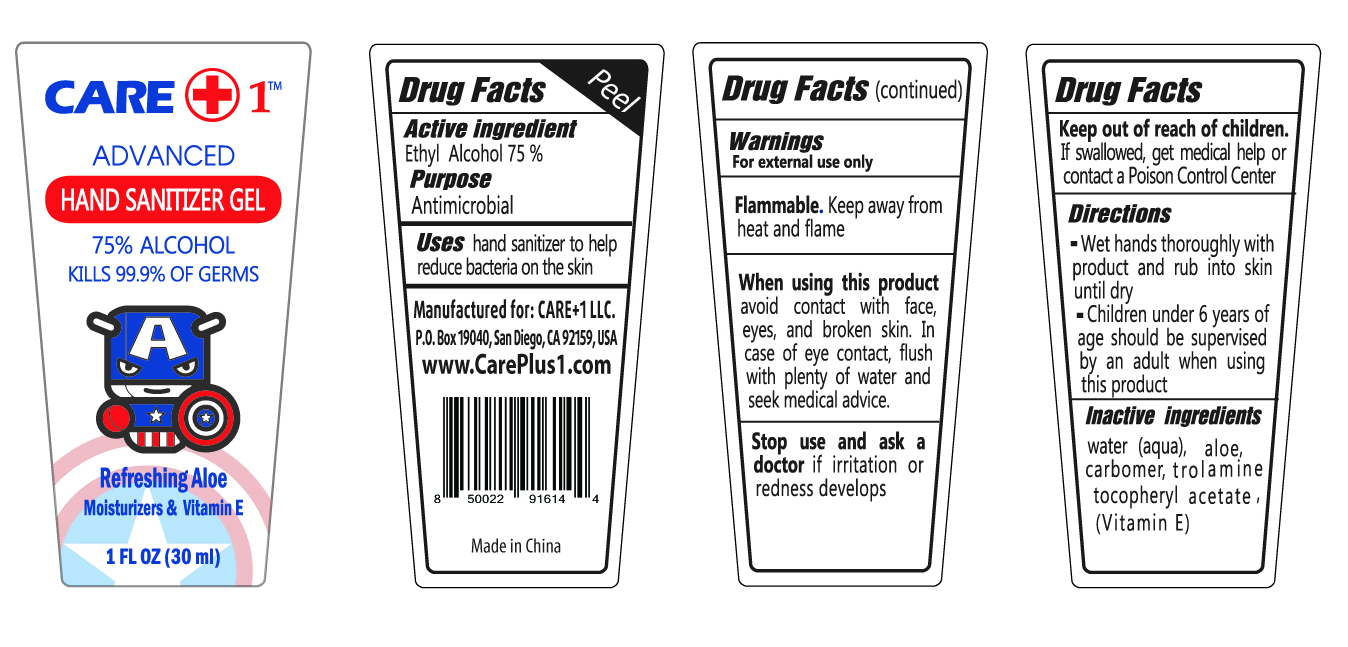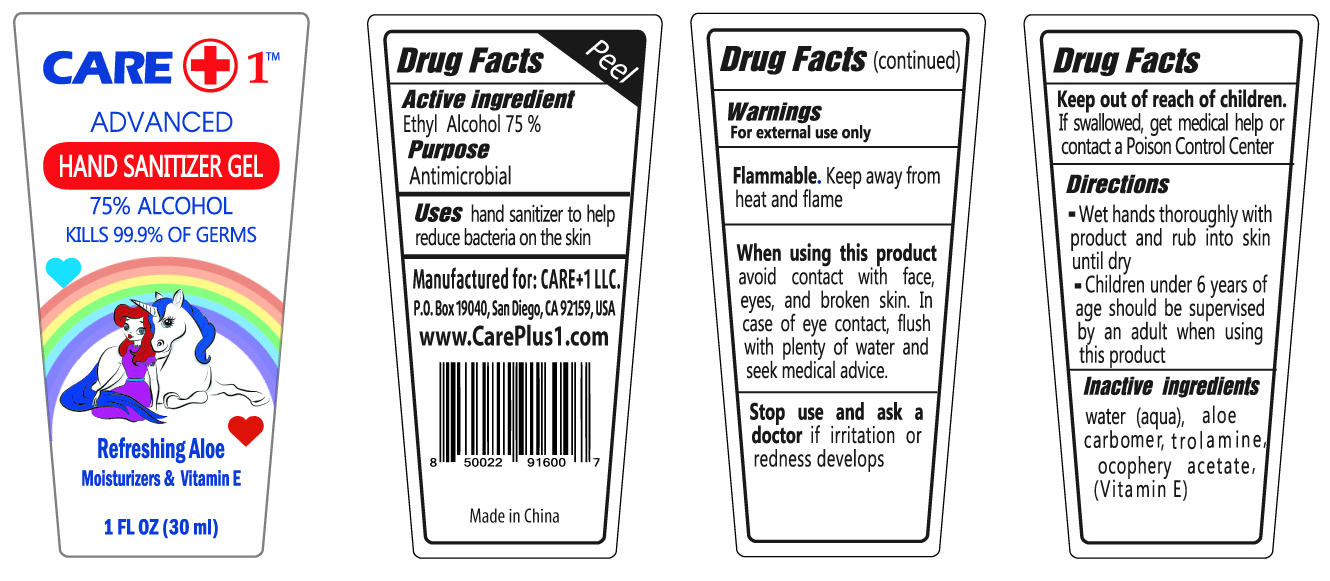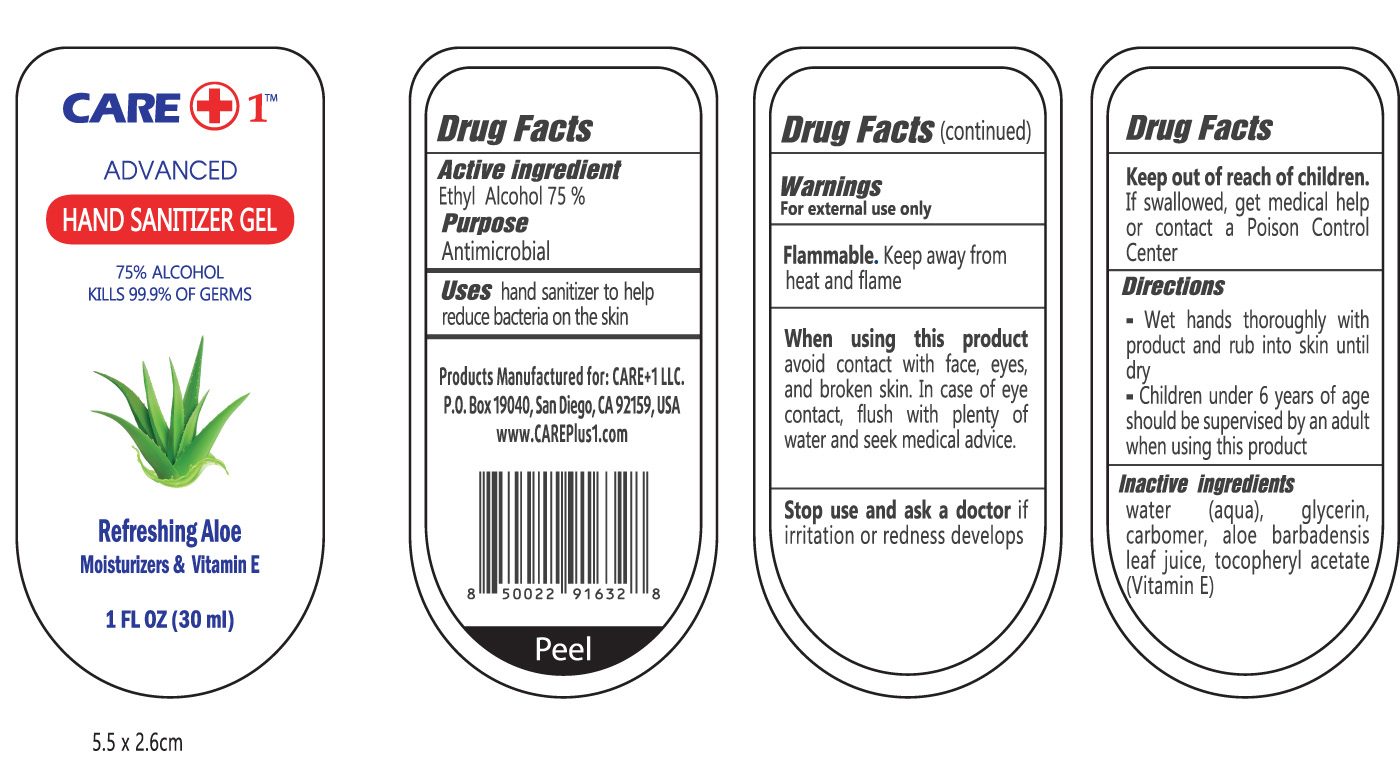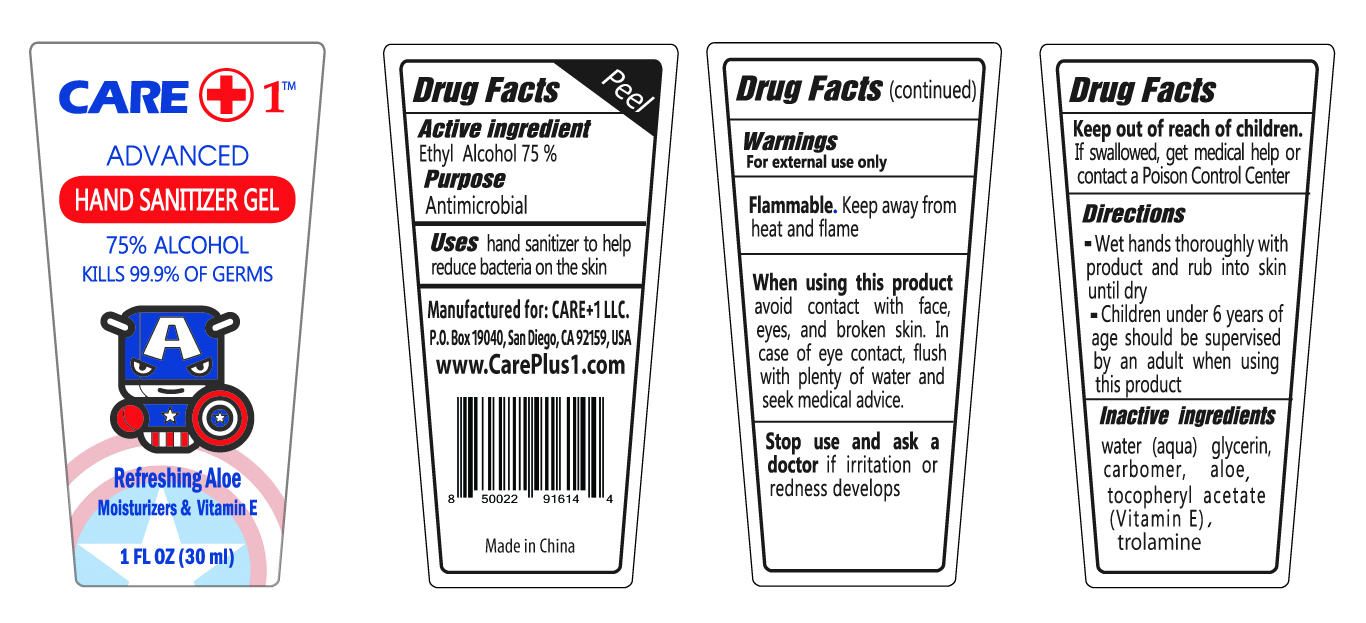 DRUG LABEL: Hand Sanitizer Gel
NDC: 80072-003 | Form: GEL
Manufacturer: CARE + 1 LLC
Category: otc | Type: HUMAN OTC DRUG LABEL
Date: 20201130

ACTIVE INGREDIENTS: ALCOHOL 75 mL/100 mL
INACTIVE INGREDIENTS: ALOE 0.0005 mL/100 mL; TROLAMINE 0.001 mL/100 mL; WATER 0.24 mL/100 mL; CARBOMER HOMOPOLYMER, UNSPECIFIED TYPE 0.002 mL/100 mL

HAND SANITIZER GEL

Active Ingredient(s)

Alcohol 75%

Purpose

Antimicrobial

Use

Hand Sanitizer to help reduce bacteria on the skin

Warnings

For external use only. Flammable. Keep away from heat or flame

When using this product

Avoid contact with face, eyes and broken skin. In case of contact with eyes, flush with plenty of water and seek medical advice.

Stop use and ask a doctor if irritation or rash occurs. These may be signs of a serious condition.

Keep out of reach of children. If swallowed, get medical help or contact a Poison Control Center

Directions

- Wet hands thoroughly with product and rub into skin until dry.
- Children under 6 years of age should be supervised by an adult when using this product.

Inactive ingredients

water (aqua), Aloe, Carbomer, Tocopheryl Acetate (Vitamin E), Trolamine

Hand Sanitizer Gel Bottle - 1 FL OZ - 30 Ml